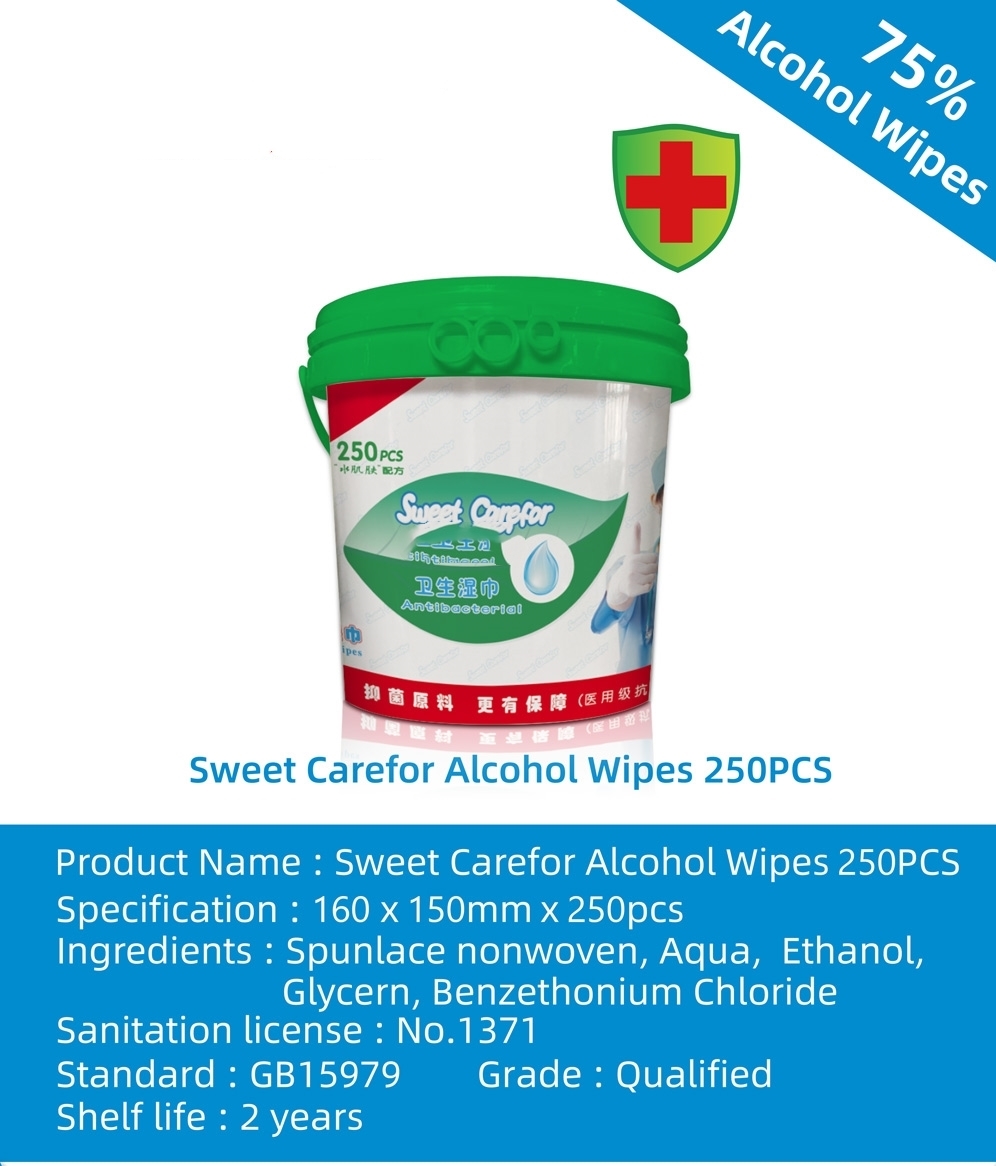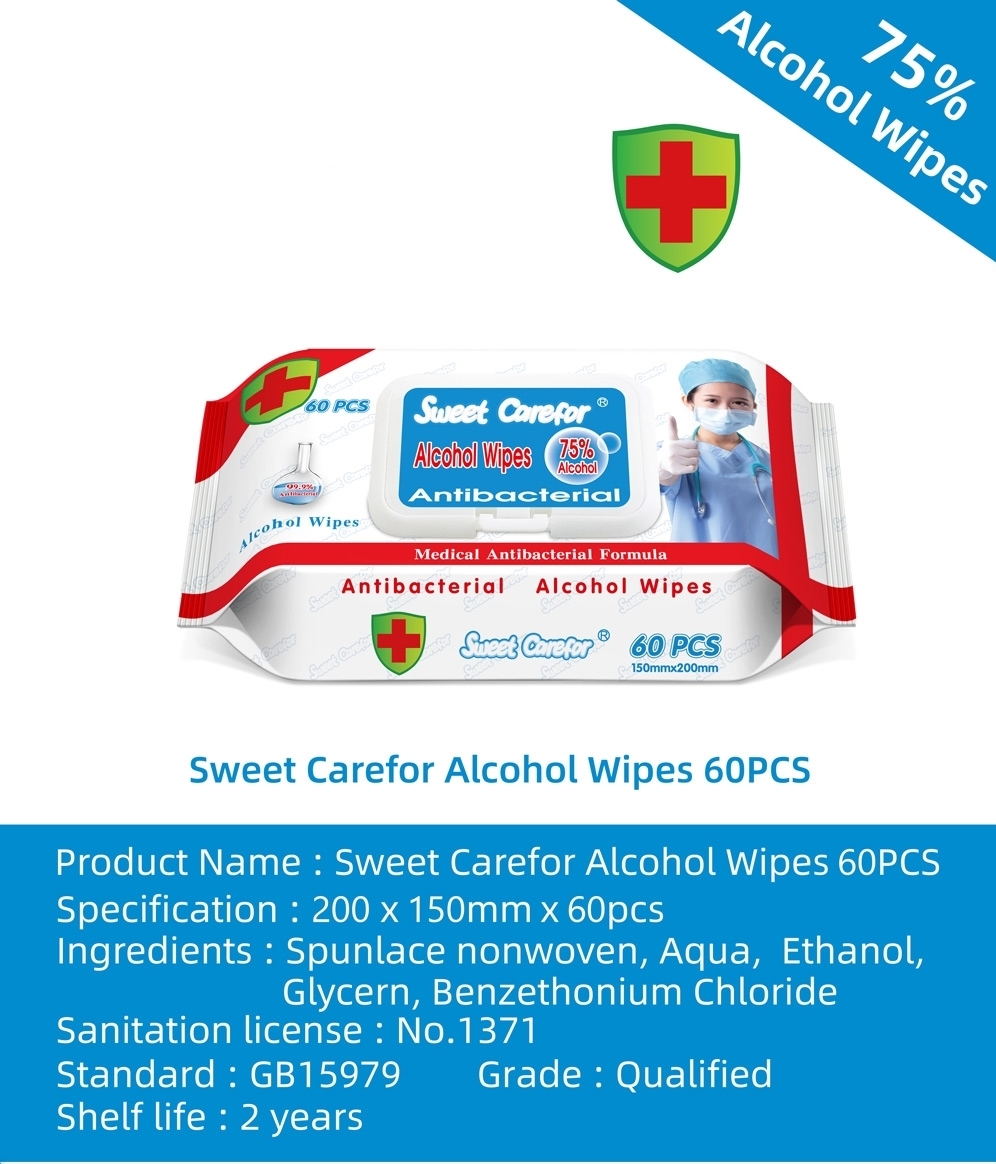 DRUG LABEL: ALCOHOL WIPES
NDC: 50536-103 | Form: SOLUTION
Manufacturer: AMERICAN CHEMICAL AND SANITARY SUPPLY INC
Category: otc | Type: HUMAN OTC DRUG LABEL
Date: 20240509

ACTIVE INGREDIENTS: ALCOHOL 7.5 mL/1 1
INACTIVE INGREDIENTS: WATER; GLYCERIN; BENZETHONIUM CHLORIDE

AMERICAN CHEMICAL AND SANITARY SUPPLY - SWEET CARE FOR ALCOHOL WIPES (50536-103)

ACTIVE INGREDIENT

ALCOHOL 75%

PURPOSE

ANTIBACTERIAL

USES

ANTIBACTERIAL ALCOHOL WIPES

WARNINGS

FOR EXTERNAL USE ONLY

Keep out of reach of children.

DIRECTIONS

SUITABLE FOR CLEANSING AND HYGIENE FOR HOSPITAL MEDICAL STAFF AND NURSING STAFF, PUBLIC AREAS, HOUSEHOLD, PERSONAL CARE, AND SURFACES HYGIENE AND DISINFECTION DURING FLU SEASON.

INACTIVE INGREDIENTS

WATER, GLYCERIN, BENZETHONIUM CHLORIDE